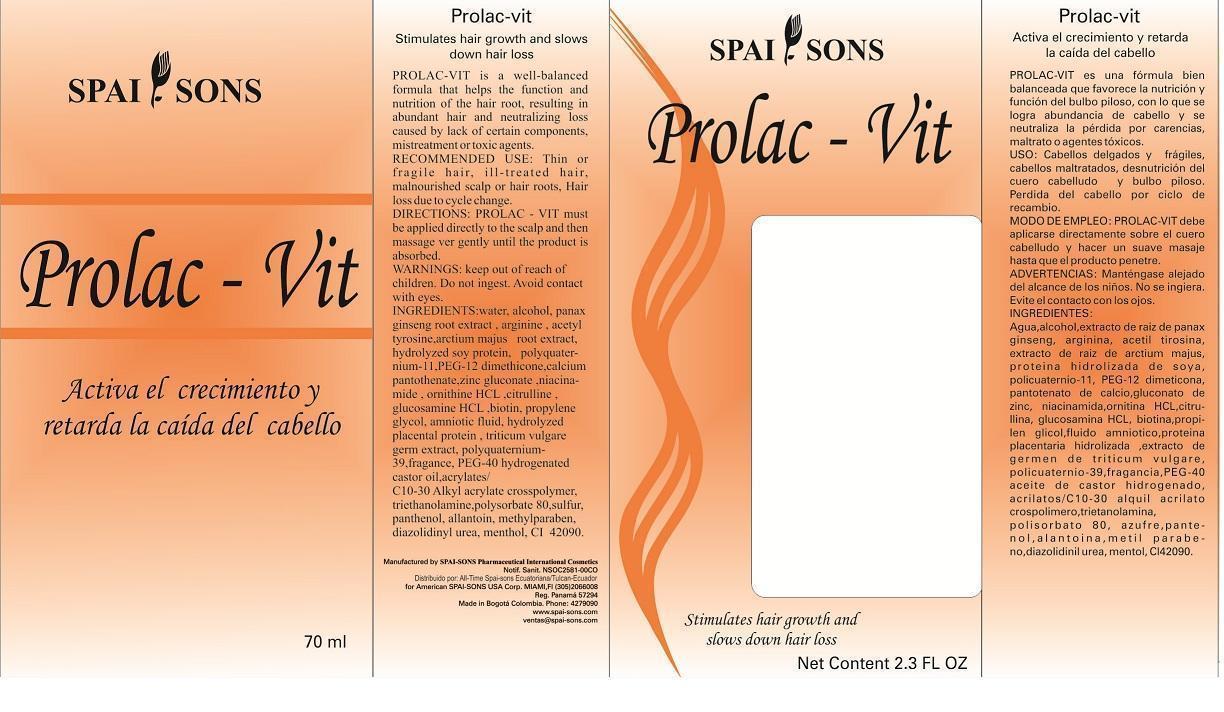 DRUG LABEL: SPAI-SONS
NDC: 66854-007 | Form: LIQUID
Manufacturer: SPAI-SONS PHARMACEUTICAL INTERNATIONAL COSMETICS
Category: prescription | Type: HUMAN PRESCRIPTION DRUG LABEL
Date: 20120805

ACTIVE INGREDIENTS: BIOTIN 0.01 mg/100 mL
INACTIVE INGREDIENTS: WATER; ALCOHOL; ASIAN GINSENG; ARGININE; N-ACETYL-TYROSINE; ARCTIUM LAPPA ROOT; ASPARTIC ACID; HYDROXYPROLINE; THREONINE; SERINE; GLUTAMIC ACID; PROLINE; GLYCINE; ALANINE; VALINE; METHIONINE; ISOLEUCINE; LEUCINE; TYROSINE; PHENYLALANINE; HYDROXYLYSINE; ORNITHINE; LYSINE; HISTIDINE; ARGININE; TRYPTOPHAN; CYSTINE; POLYQUATERNIUM-11 (1000000 MW); PEG-12 DIMETHICONE (300 CST); CALCIUM PANTOTHENATE; ZINC GLUCONATE; NIACINAMIDE; ORNITHINE HYDROCHLORIDE; CITRULLINE; GLUCOSAMINE HYDROCHLORIDE; PROPYLENE GLYCOL; AMNIOTIC FLUID (BOVINE); HYDROLYZED PLACENTAL PROTEIN (BOVINE); WHEAT GERM; POLYQUATERNIUM-39 (35/35/30 ACRYLIC ACID/ACRYLAMIDE/DADMAC; 1500000 MW); POLYOXYL 40 HYDROGENATED CASTOR OIL; CARBOMER INTERPOLYMER TYPE A (55000 MPA.S); TROLAMINE; POLYSORBATE 80; SULFUR; PANTHENOL; ALLANTOIN; METHYLPARABEN; DIAZOLIDINYL UREA; MENTHOL; FD&C BLUE NO. 1

SPAI-SONS PROLAC-VIT

ACTIVE INGREDIENT

Biotin is a major component of the formulation acts to strengthen the hair follicle and prevents hair loss as well. It is nutrient for the hair root oxygenate the hair turn slowing the loss. Provides resilience and resistence to hair. Addition of biotin are other ingredient such as Asian Ginseng, Arginine, Zinc Gluconate, Niacinamide, Ornitine HCl, and Citrulline which help strengthen the hair follicle and produce a synergistic action on it.

PURPOSE

Prolac-vit is a well balanced formula that helps the function and nutrition of hair root, resulting in abundant hair and neutralizing alopecia caused by lack and certain components, mistreatment or toxic agents.

KEEP OUT OF REACH OF CHILDREN

This product must be keep out reach of children

INDICATIONS AND USAGE

This product is for topical application directly on the hair follicle.

WARNINGS

Avoid contact with eyes, if they do wash with water. If swallowed contact a physician immediately

DOSAGE AND ADMINISTRATION

Recommended use: thin or fragile, ill-treated hair, malnourished scalp or hair roots, Alopecia, hair loss due to cycle change.

Directions: must be applied directly to the scalp and then massage very gently until the product is absorbed

INACTIVE INGREDIENT

This is a liquid prepared with the technology needed to provide the hair follicle absorption of the active ingredients, plus inactive ingredients contribute to the regeneration of the hair fiber by providing a strengthening therefore. No adverse effects were seen with the use of this product as inactive ingredients do not cause skin hypersensivity.

IMAGE OF CARTON LABEL